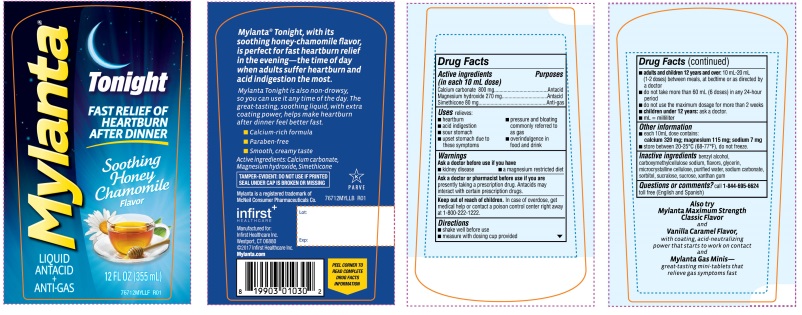 DRUG LABEL: Mylanta New Tonight Soothing Honey Chamomile
NDC: 62372-510 | Form: SUSPENSION
Manufacturer: Infirst Healthcare Inc.
Category: otc | Type: HUMAN OTC DRUG LABEL
Date: 20241211

ACTIVE INGREDIENTS: CALCIUM CARBONATE 800 mg/10 mL; MAGNESIUM HYDROXIDE 270 mg/10 mL; DIMETHICONE 80 mg/10 mL
INACTIVE INGREDIENTS: BENZYL ALCOHOL; GLYCERIN; MICROCRYSTALLINE CELLULOSE; WATER; SODIUM CARBONATE; CARBOXYMETHYLCELLULOSE SODIUM, UNSPECIFIED FORM; SORBITOL; SUCRALOSE; SUCROSE; XANTHAN GUM

Mylanta Tonight Soothing Honey Chamomile Flavor 12 FL OZ

Active ingredients (in each 10 mL dose)

Calcium carbonate 800 mg

Magnesium hydroxide 270 mg
Simethicone 80 mg

Purpose

Antacid

Antacid
Anti-gas

Uses

relieves:

- heartburn
- pressure and bloating commonly referred to as gas
- acid indigestion
- sour stomach
- upset stomach due to these symptoms
- overindulgence in food and drink

Warnings

Ask a doctor before use if you have
• kidney disease • a magnesium restricted diet

Ask a doctor before use if you have

• kidney disease • a magnesium restricted diet

Ask a doctor or pharmacist before use if you are

presently taking a prescription drug. Antacids may interact with certain prescription drugs.

Keep out of reach of children.

In case of overdose, get medical help
or contact a poison control center right away at 1-800-222-1222.

Directions

- shake well before use
- measure with dosing cup provided
- adults and children 12 years and over: 10 mL-20 mL (1-2 doses) between meals, at bedtime or as directed by a doctor
- do not take more than 60 mL (6 doses) in any 24- hour period
- do not use the maximum dosage for more than 2 weeks
- children under 12 years: ask a doctor
- mL= milliliter

Other information

•each 10 mL dose contains:

calcium 320 mg; magnesium 115mg; sodium 7 mg

• store between 20-25°C (68-77°F), do not freeze.

Inactive ingredients

benzyl alcohol, carboxymethylcellulose sodium, flavors, glycerin, microcrystalline cellulose, purified water, sodium carbonate, sorbitol, sucralose, sucrose, xanthan gum

Questions or comments?

call 1-844-695-6624toll free (English and Spanish)

Principal Display Panel

MYLANTA ®

LIQUID Tonight

ANTACID + ANTI-GAS

FAST RELIEF OF HEARTBURN AFTER DINNER

Soothing Honey Chamomile Flavor

12 FL OZ (355mL)

Mylanta Tonight, with its soothing honey- chamomile flavor, is perfect for fast heartburn relief in the evening-the time of day when adults suffer heartburn and acid indigestion the most.

Mylanta Tonight is also non–drowsy, so you can use it any time of the day. The great-tasting, soothing liquid, with extra coating power, helps make after-dinner heartburn feel better fast.

- Calcium-rich formula
- Paraben-free
- Smooth, creamy taste

Active ingredients: Calcium carbonate, Magnesium hydroxide, Simethicone

TAMPER-EVIDENT: DO NOT USE IF PRINTED SEAL UNDER CAP IS BROKEN OR MISSING

Mylanta is a registered trademark of McNeil Consumer Pharmaceuticals Co.

infirst^+

HEALTHCARE

Manufactured for:

Infirst Healthcare Inc.

Westport, CT 06880

©2017 Infirst Healthcare Inc.

Mylanta.com